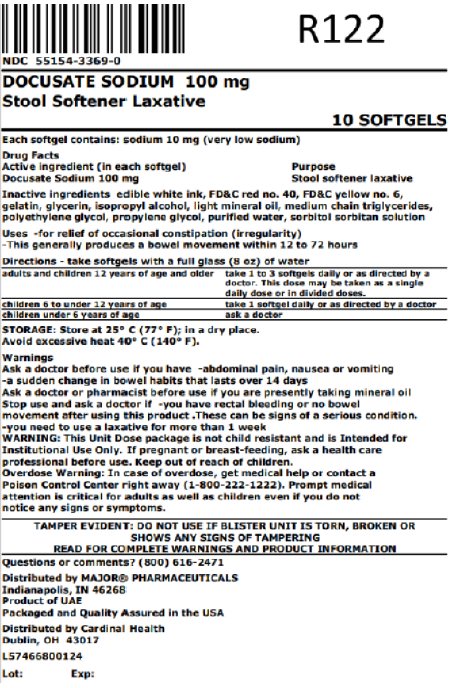 DRUG LABEL: Docusate Sodium - Stool Softener Laxative
NDC: 55154-3369 | Form: CAPSULE, LIQUID FILLED
Manufacturer: Cardinal Health 107, LLC
Category: otc | Type: HUMAN OTC DRUG LABEL
Date: 20251002

ACTIVE INGREDIENTS: DOCUSATE SODIUM 100 mg/1 1
INACTIVE INGREDIENTS: FD&C RED NO. 40; FD&C YELLOW NO. 6; GELATIN, UNSPECIFIED; GLYCERIN; ISOPROPYL ALCOHOL; LIGHT MINERAL OIL; MEDIUM-CHAIN TRIGLYCERIDES; POLYETHYLENE GLYCOL, UNSPECIFIED; PROPYLENE GLYCOL; WATER; SORBITOL; SORBITAN

Docusate Sodium - Stool Softener Laxative

Active ingredient (in each softgel)

Docusate Sodium 100 mg

Purpose

Stool softener laxative

Uses

• for relief of occasional constipation (irregularity)
• This generally produces a bowel movement within 12 to 72 hours.

Warnings

Ask a doctor before use if you have
• abdominal pain, nausea, or vomiting
• a sudden change in bowel habits that lasts over 14 days

Ask a doctor or pharmacist before use if you are presently taking mineral oil

Stop use and ask a doctor if
• you have rectal bleeding or no bowel movement after using this product.
These can be signs of a serious condition
• you need to use a laxative for more than 1 week

If pregnant or breast-feeding, ask a health care professional before use.

Keep out of reach of children
Overdose Warning: In case of overdose, get medical help or contact a Poison Control Center right away (1-800-222-1222). Prompt medical attention is critical for adults as well as children even if you do not notice any signs or symptoms.

Directions

• take softgels with a full glass (8 oz) of water

adults and children 12 years of age and older | take 1 to 3 softgels daily or as directed by a doctor. This dose may be taken as a single daily dose or in divided doses.
children 6 to under 12 years of age | take 1 softgel daily or as directed by a doctor
children under 6 years of age | ask a doctor

Other information

• each softgel contains: sodium 10 mg (very low sodium)
• store at 25°C (77°F) in a dry place. Avoid excessive heat 40°C (140°F).

Overbagged with 10 liquid-filled capsules per bag, NDC 55154-3369-0

WARNING: This Unit Dose package is not child resistant and is Intended for Institutional Use Only. Keep this and all drugs out of the reach of children.

Inactive ingredients

edible white ink, FD&C red no. 40, FD&C yellow no. 6, gelatin, glycerin, isopropyl alcohol, light mineral oil, medium chain triglycerides, polyethylene glycol, propylene glycol, purified water, sorbitol sorbitan solution

Questions or comments?

(800)616-2471

MAJOR®

Unit Dose

TAMPER EVIDENT: DO NOT USE IF PACKAGE IS OPENED OR IF BLISTER UNIT IS TORN, BROKEN OR SHOWS ANY SIGNS OF TAMPERING

READ AND KEEP OUTER CARTON FOR COMPLETE WARNINGS AND PRODUCT INFORMATION

Distributed by:
MAJOR® PHARMACEUTICALS
Indianapolis, IN 46268

Distributed By:

Cardinal Health

Dublin, OH 43017

L57466800124

Product of UAE
Packaged and Quality Assured in the USA

CT0904718361

REV.01-032022

Principal Display Panel

NDC 55154-3369-0

DOCUSATE SODIUM 100 mg

Stool Softener Laxative

10 SOFTGELS